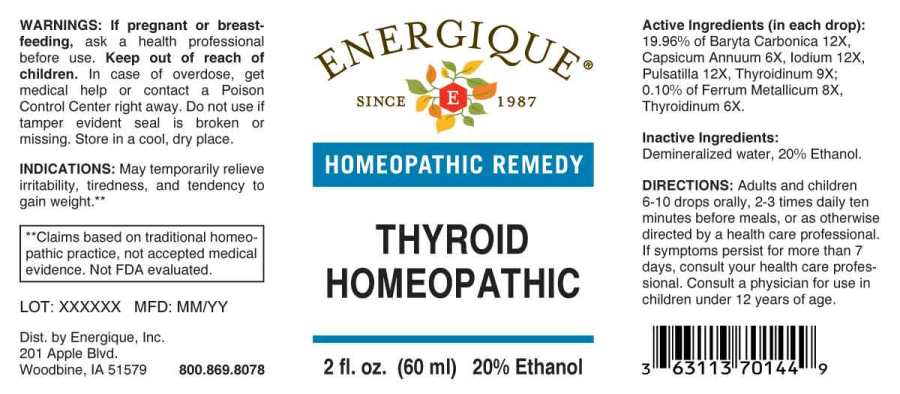 DRUG LABEL: Thyroid Homeopathic
NDC: 44911-0505 | Form: LIQUID
Manufacturer: Energique, Inc.
Category: homeopathic | Type: HUMAN OTC DRUG LABEL
Date: 20230616

ACTIVE INGREDIENTS: CAPSICUM 6 [hp_X]/1 mL; SUS SCROFA THYROID 6 [hp_X]/1 mL; IRON 8 [hp_X]/1 mL; BARIUM CARBONATE 12 [hp_X]/1 mL; IODINE 12 [hp_X]/1 mL; PULSATILLA PRATENSIS WHOLE 12 [hp_X]/1 mL
INACTIVE INGREDIENTS: WATER; ALCOHOL

Drug Facts:

ACTIVE INGREDIENTS:

(in each drop): 19.96% of Baryta Carbonica 12X, Capsicum Annuum 6X, Iodium 12X, Pulsatilla (Pratensis) 12X, Thyroidinum (Suis) 9X; 0.10% of Ferrum Metallicum 8X, Thyroidinum (Suis) 6X.

INDICATIONS:

May temporarily relieve irritability, tiredness, and tendency to gain weight.**

**Claims based on traditional homeopathic practice, not accepted medical evidence. Not FDA evaluated.

WARNINGS:

If pregnant or breastfeeding, ask a health professional before use.

Keep out of reach of children. In case of overdose, get medical help or contact a Poison Control Center right away.

Do not use if tamper evident seal is broken or missing.

Store in a cool, dry place.

Keep out of reach of children. In case of overdose, get medical help or contact a Poison Control Center right away.

DIRECTIONS:

Adults and children 6 to 10 drops orally, 2-3 times daily ten minutes before meals, or as otherwise directed by a health care professional. If symptoms persist for more than 7 days, consult your health care professional. Consult a physician for use in children under 12 years of age.

INDICATIONS:

May temporarily relieve irritability, tiredness, and tendency to gain weight.**

**Claims based on traditional homeopathic practice, not accepted medical evidence. Not FDA evaluated.

INACTIVE INGREDIENTS:

Demineralized water, 20% Ethanol.

QUESTIONS:

Dist. by Energique, Inc.
201 Apple Blvd.
Woodbine, IA 51579 800.869.8078

PACKAGE LABEL DISPLAY:

ENERGIQUE
SINCE 1987
HOMEOPATHIC REMEDY
THYROID
HOMEOPATHIC
2 fl. oz. (60 ml)